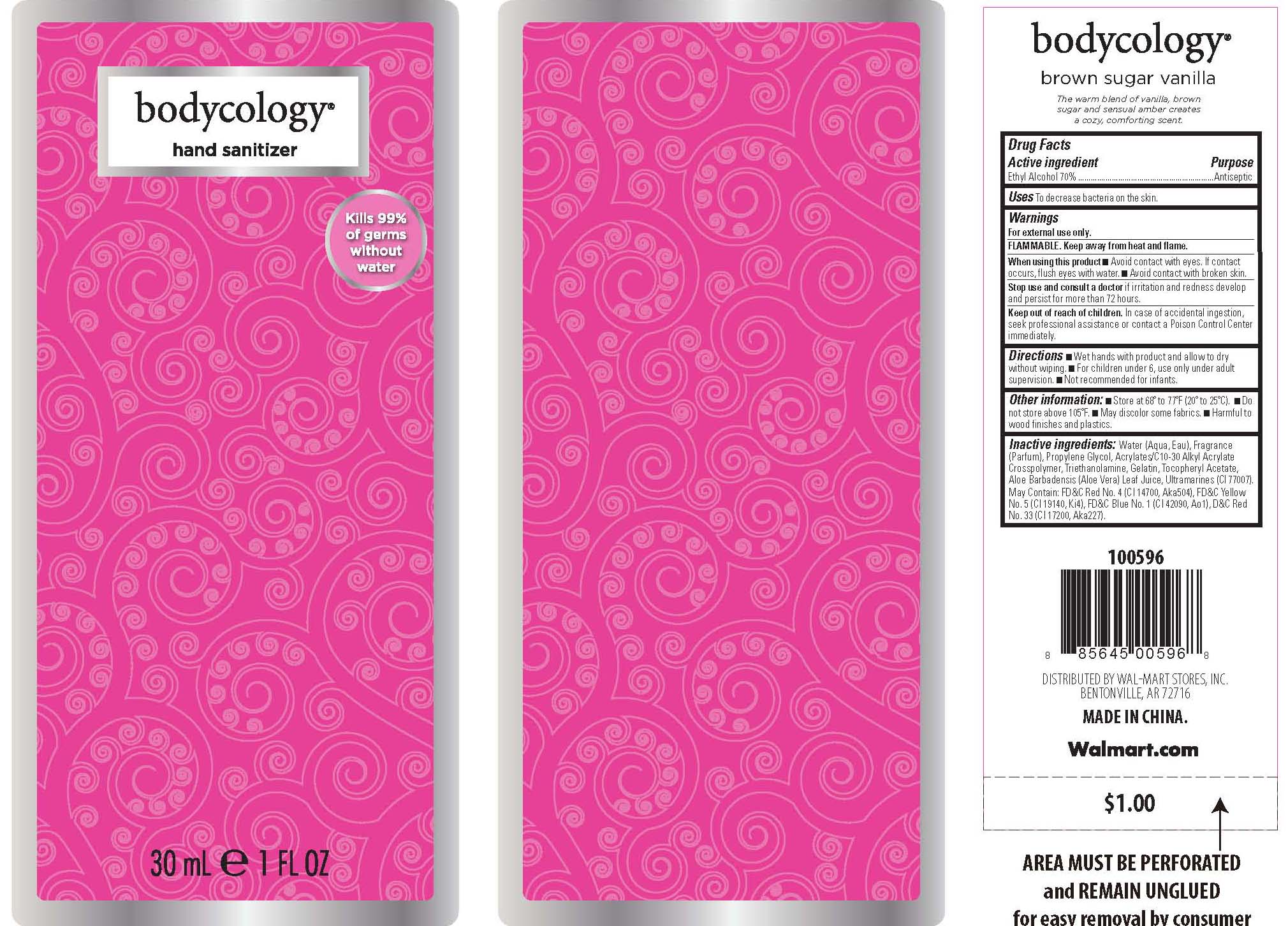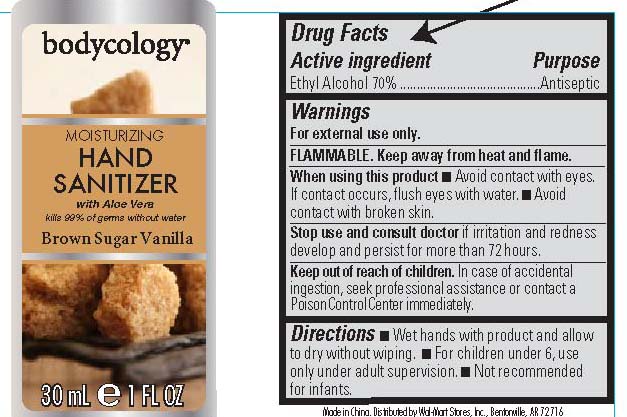 DRUG LABEL: Bodycology
NDC: 49035-568 | Form: GEL
Manufacturer: Wal-Mart Stores, Inc.
Category: otc | Type: HUMAN OTC DRUG LABEL
Date: 20110411

ACTIVE INGREDIENTS: ALCOHOL 70 mL/100 mL
INACTIVE INGREDIENTS: WATER; PROPYLENE GLYCOL; CARBOMER INTERPOLYMER TYPE A (55000 MPA.S)); TROLAMINE; GELATIN; ALOE VERA LEAF; FD&C RED NO. 4; FD&C YELLOW NO. 5; FD&C BLUE NO. 1; D&C RED NO. 33

Brown Sugar Vanilla Hand Sanitizer

Active Ingredient purpose
Ethyl Alcohol 70% Antiseptic

PURPOSE

to decrease bacteria on the skin.

Keep out of reach of children.

Stop use and consult a doctor if irritation and redness develop and persist for more than 72 hours.

Warnings: For external use only.
Flammable. Keep away from heat and flame.
When using this product: Avoid contact with eyes. If contact occurs, flush eyes with water. Avoid contact with broken skin.
In case of accidental ingestion, seek professional assistance or contact a Poison Control Center immediately.

DOSAGE AND ADMINISTRATION

Directions: Wet hands with product and allow to dry without wiping.
For children under 6, use only under adult supervision. Not recommended
for infants.

INACTIVE INGREDIENT

nactive ingredients: Water (aqua, eau), fragrance (parfum), Propylene Glycol, Acrylates/C10-30 alkyl acrylate crosspolymer, triethanolamine, Gelatin, Tocopheryl Acetate, Aloe Barbadensis (Aloe Vera leaf juice), Ultramarines (CI77007)
May contain: FD C Red No.4(CI 14700, Aka504), FD C Yellow No. 5 (CI 19140,Ki4), FD C Blue No.1 (CI 42090, Ao1), D C Red No 33(CI 17200,Aka227)

PACKAGE LABEL

bodycology
moisturizing
hand sanitizer with aloe vera
Brown sugar vanilla
30 mL e 1 FL OZ